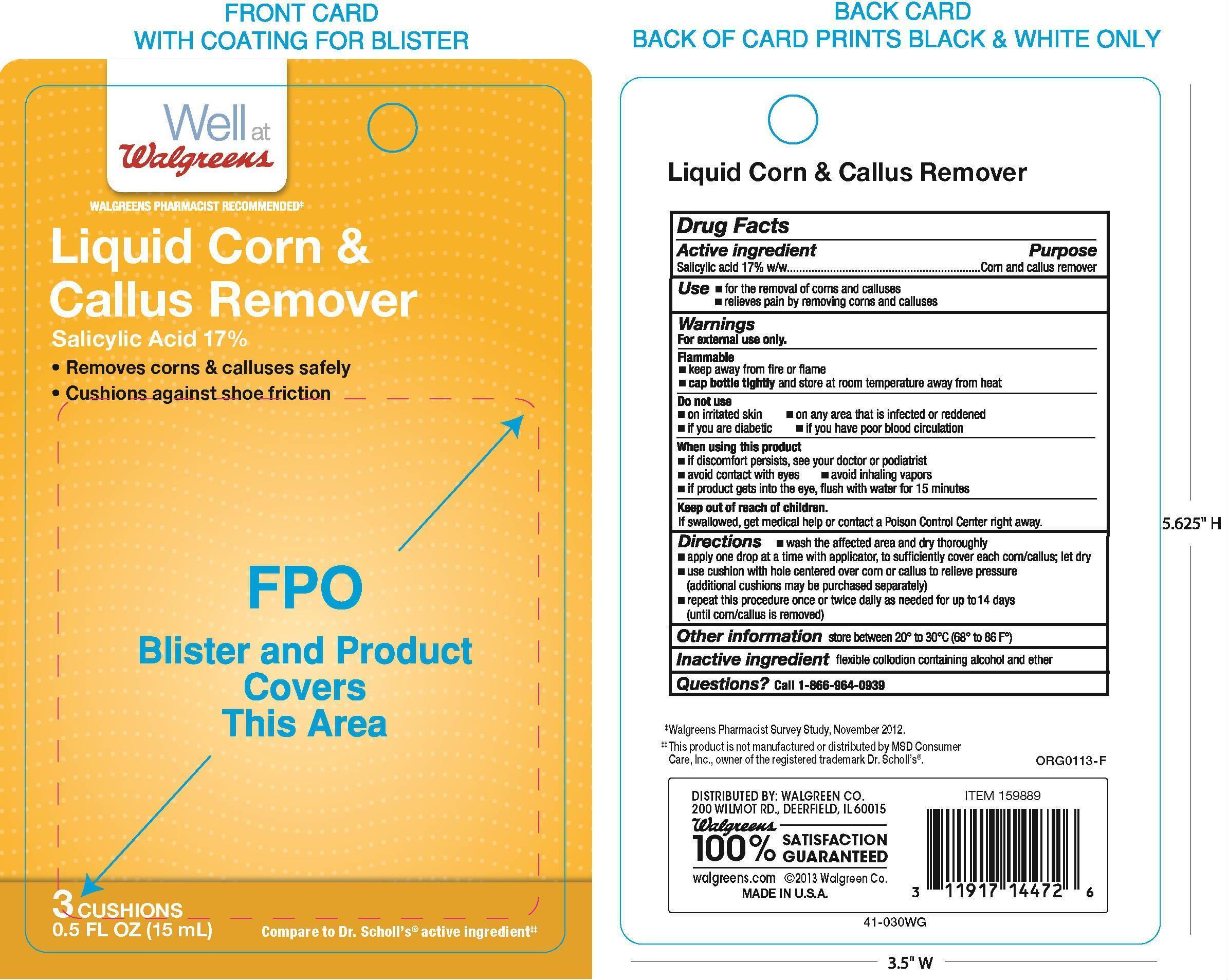 DRUG LABEL: Salicylic Acid
NDC: 0363-9889 | Form: LIQUID
Manufacturer: Walgreen Company
Category: otc | Type: HUMAN OTC DRUG LABEL
Date: 20251008

ACTIVE INGREDIENTS: SALICYLIC ACID 0.17 g/1 g
INACTIVE INGREDIENTS: PYROXYLIN; CAMPHOR (NATURAL); CASTOR OIL

Walgreens Liquid Corn and Callus Remover

Active ingredient

Salicylic acid 17%w/w

Purpose

Corn and callus remover

Uses

- for the removal of corns and calluses
- relieves pain by removing corns and calluses

Warnings

For external use only.

Flammable

- keep away from fire or flame
- cap bottle tightly and store at room temperature away heat

Do not use

- on irritated skin
- on any area that is infected or reddened
- if you are a diabetic
- if you have poor blood circulation

When using this product

- if discomfort persists, see your doctor or podiatrist
- avoid contact with eyes
- avoid inhaling vapors
- if product gets into the eyes, flush with water for 15 minutes

Keep out of reach of children.

If swallowed, get medical help or contact a Poison Control Center right away.

Directions

- wash affected area and dry thoroughly
- apply one drop at a time with applicator, to sufficiently cover each corn/callus; let dry
- use cushions with hole centered over corn or callus to relieve pressure (additional cushions may be purchased separately)
- repeat this procedure once or twice daily as needed for up to 14 days (until corn/callus is removed)

Other information

store between 20°C to 30°C (68°F to 86°F)

Inactive ingredients

camphor, castro oil, ethanol, ethyl ether, nitrocellulose

Questions?

Call 1-866-964-0939

Principal Display Panel

Well at Walgreens
Liquid Corn & Callus Remover
Salicylic Acid 17%

- Removes corn & calluses safely
- Cushions against shoe friction

3 Cushions

0.5 FL OZ (15mL)